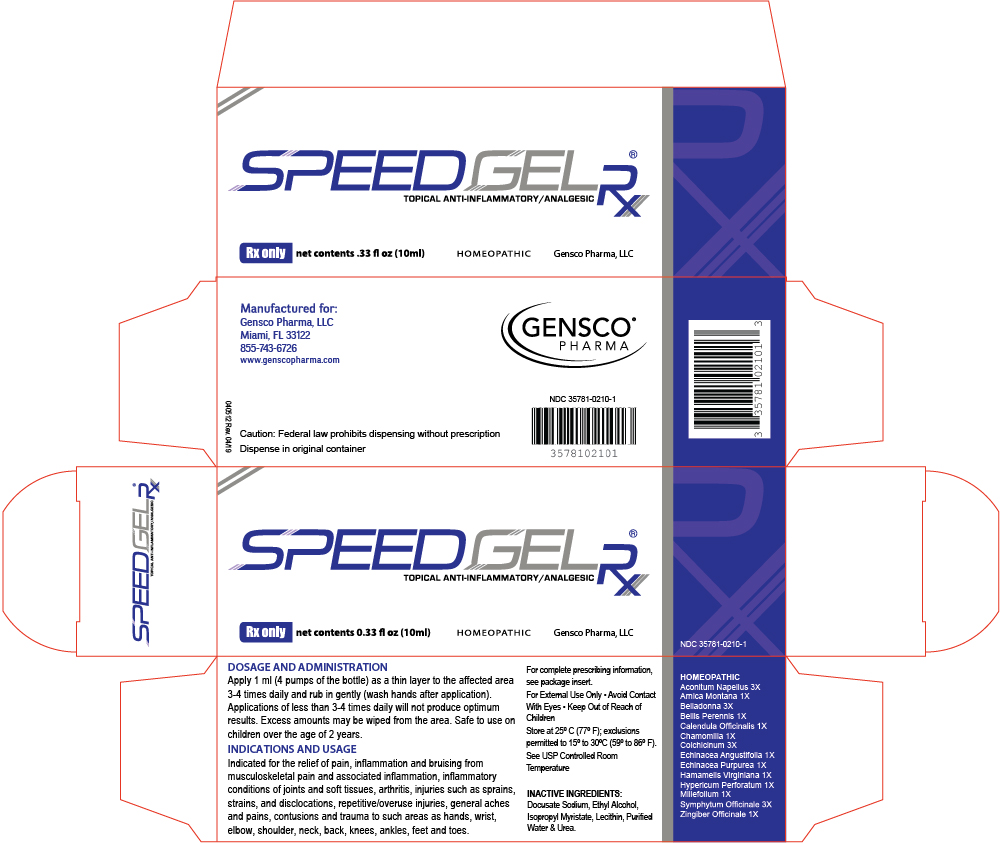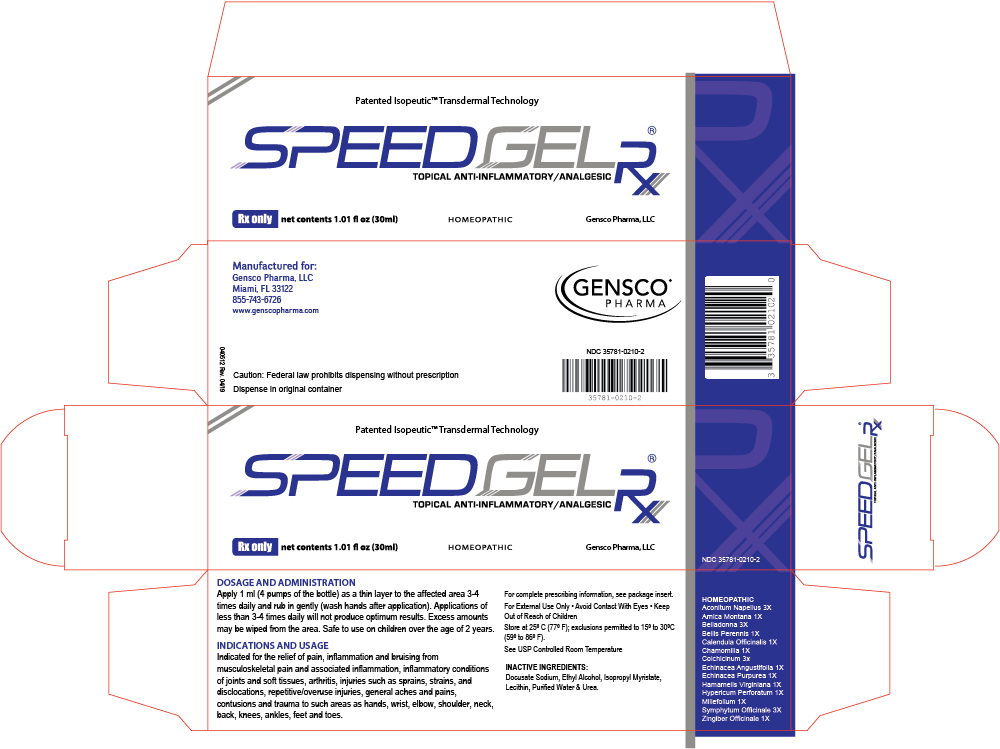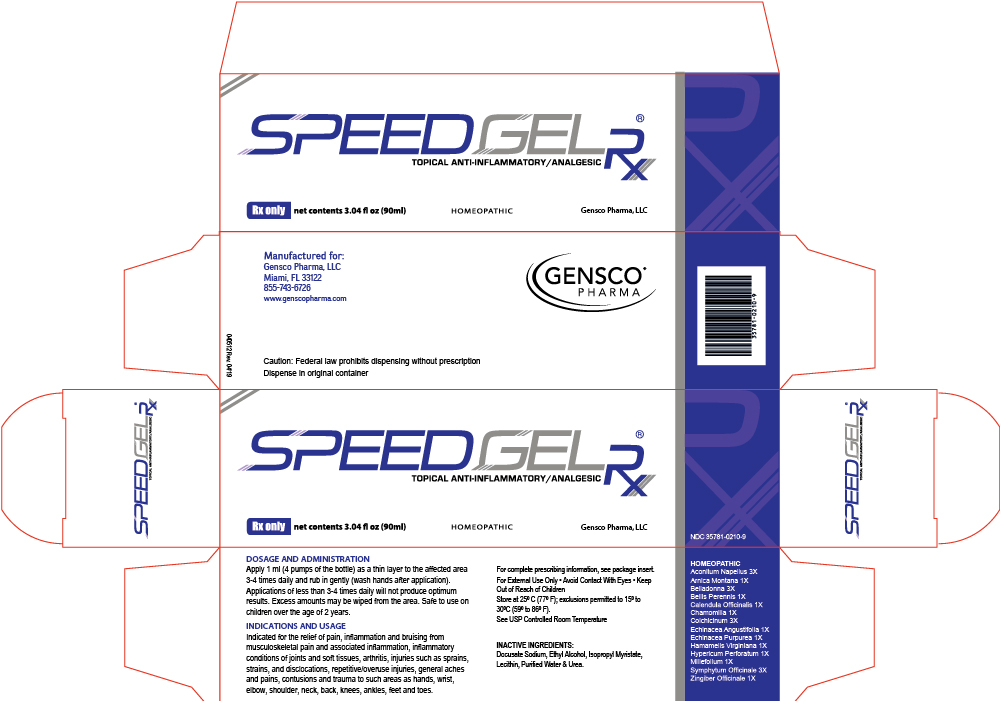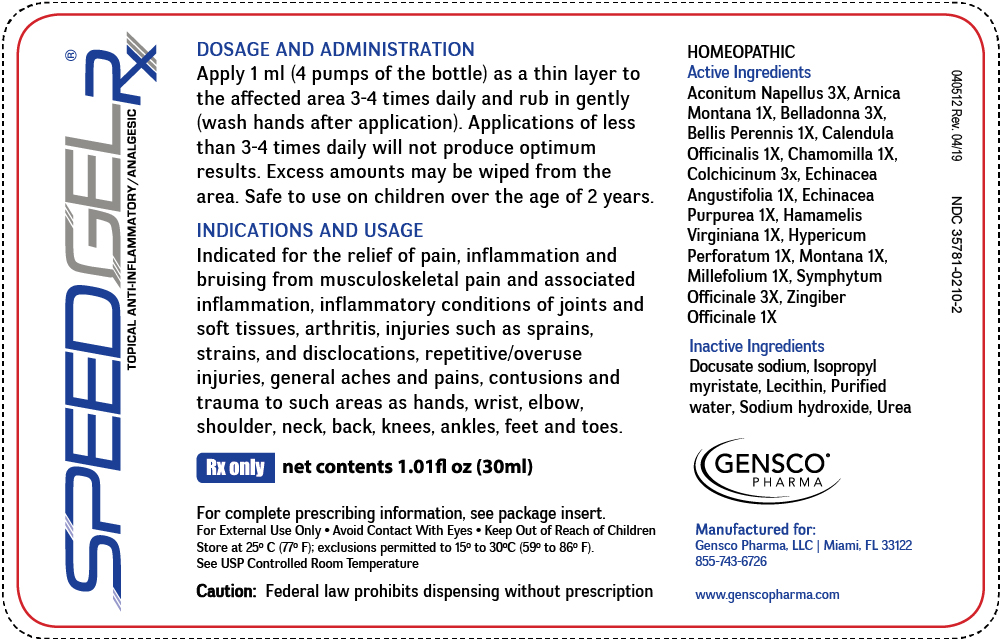 DRUG LABEL: SPEEDGEL RX
NDC: 35781-0210 | Form: GEL
Manufacturer: Gensco Laboratories, LLC
Category: homeopathic | Type: HUMAN PRESCRIPTION DRUG LABEL
Date: 20221005

ACTIVE INGREDIENTS: ECHINACEA ANGUSTIFOLIA 1 [hp_X]/30 mL; ECHINACEA PURPUREA 1 [hp_X]/30 mL; ACONITUM NAPELLUS 3 [hp_X]/30 mL; ARNICA MONTANA 1 [hp_X]/30 mL; CALENDULA OFFICINALIS FLOWERING TOP 1 [hp_X]/30 mL; HAMAMELIS VIRGINIANA ROOT BARK/STEM BARK 1 [hp_X]/30 mL; ATROPA BELLADONNA 3 [hp_X]/30 mL; BELLIS PERENNIS 1 [hp_X]/30 mL; CHAMOMILE 1 [hp_X]/30 mL; ACHILLEA MILLEFOLIUM 1 [hp_X]/30 mL; HYPERICUM OIL 1 [hp_X]/30 mL; COMFREY ROOT 3 [hp_X]/30 mL; COLCHICINE 3 [hp_X]/30 mL; GINGER 1 [hp_X]/30 mL
INACTIVE INGREDIENTS: WATER; ISOPROPYL MYRISTATE; LECITHIN, SOYBEAN; UREA; DOCUSATE SODIUM; SODIUM HYDROXIDE

SPEEDGEL RX
TOPICAL ANTI-INFLAMATORY/ANALGESIC

DESCRIPTION

SpeedGel Rx® is a prescription transdermal gel that provides relief of pain, inflammation and bruising, utilizing patented Isopeutic™
Transdermal Technology. The Gensco® patented transdermal drug delivery system used in SpeedGel Rx® carries proprietary formulation of
active ingredients, through the skin to the locally affected tissues. SpeedGel Rx® is applied directly to the affected site specifically,
minimizing side effects, interactions and comorbidities caused by oral
therapies and topical NSAIDs. Furthermore, SpeedGel Rx® is clinically
proven to reduce narcotic use.

SpeedGel Rx® is indicated for the relief of pain, inflammation and bruising from musculoskeletal pain and associated inflammation, inflammatory conditions of joints and soft tissues, arthritis, injuries such as sprains, strains, and disclocations, repetitive/overuse injuries, general aches and pains, contusions and trauma to such areas as hands, wrist, elbow, shoulder, neck, back, knees, ankles, feet and toes. SpeedGel Rx® is a proprietary combination of 14 active ingredients, 4 of which are prescription, in a patented transdermal delivery system. Among the prescription ingredients is Colchicinum Autumnale also known as Colchicine, which is a well-known, strong and effective anti-inflammatory medication.

It contains the following active ingredients:
Aconitum Napellus 3X HPUS, Arnica Montana 1X HPUS, Belladonna 3X
HPUS, Bellis Perennis 1X HPUS, Calendula Officinalis 1X HPUS,
Chamomilla 1X HPUS, Colchicinum 3X HPUS, Echinacea Angustifolia
1X HPUS, Echinacea Purpurea 1X HPUS, Hamamelis Virginiana 1X
HPUS, Hypericum Perforatum 1X HPUS, Millefolium 1X HPUS,
Symphytum Officinale 3X HPUS, Zingiber Officinale 1X HPUS.

It also contains the following inactive ingredients:
Docusate sodium, Ethyl Alcohol, Isopropyl myristate, Lecithin, Purified
Water & Urea.

The patented transdermal gel’s liposomal base comprising of hydrophilic and lipophilic components is designed to suspend the active ingredients and allow for the hydration of the skin barrier and movement of the active ingredients, irrespective of their molecular polarity, across the skin at an enhanced rate. The unique transdermal characteristics in SpeedGel Rx® permit the active ingredients to penetrate to the site of injury, diminishing pain and inflammation, and enhancing bruise resolution. As a topically applied transdermal medication, SpeedGel Rx® avoids the common concerns of toxicity and drug interactions associated with systemic (oral) medications.

SpeedGel Rx® is an amber colored, odorless gel dispensed in a patented metered dose container (MDose) containing either 10ml, 30ml, or 90ml. Gensco’s unique metered dose technology (MDose™) which dispenses exactly (0.25 mL of medication per pump) per application, covering a 2”x2” area of skin. MDose provides more accurate dosing, less waste and significant cost savings (Gensco® Pharma Tube vs. Pump Study).

CLINICAL PHARMACOLOGY

SpeedGel Rx® is a drug under FDA regulation and HPUS monograph. The active ingredients of SpeedGel Rx® are listed and described within
the Homeopathic Pharmacopeia of the United States (HPUS), the official FDA compendium of homeopathic drugs.

The Homeopathic Pharmacopeia of the United States (HPUS), the officially recognized FDA reference source for homeopathic compounds
in the U.S., identifies the ingredients of SpeedGel Rx® as shown in TABLE 1.:

Ingredients | Common Name | Indications
Aconitum Napellus | Monk’s-hood | Neuralgia, rheumatism,; hemostasis, analgesia
Arnica Montana | Mountain arnica | Stimulates healing of injured; tissues, wounds, contusions,; hematomas, neuralgia, myalgia,; analgesia
Belladonna | Deadly nightshade | Inflammation locally
Bellis Perennis | Daisy | Dislocations, bruising,; reducing edema
Calendula Officinalis | Calendula | Analgesia, inflammation
Colchicinum | Colchicine | Inflammation and gout
Chamomilla | Chamomile | Inflammation, promotes; healing of tissues
Echinacea Angustifolia | Narrow leaf cone flower | Inflammation and inhibits; hyaluronidase
Echinacea Purpurea | Purple cone flower | Stimulates fibroblasts,; inflammation
Hamamelis Virginiana | Witch-hazel | Astringent, analgesic, hematomas
Hypericum Perforatum | St. John’s wort | Neuropathic pains
Millefolium | Yarrow | Hematomas, wound healing
Symphytum Officinale | Comfrey | Neuropathy, causalgia,; contusions, periostitis
Zingiber Officinale | Ginger | Inflammation

Bolded items are at strengths recognized by the HPUS as requiring a prescription.

INDICATIONS AND USAGE

SpeedGel Rx® is indicated for the relief of pain, inflammation and bruising from musculoskeletal pain and associated inflammation,
inflammatory conditions of joints and soft tissues, arthritis, injuries such as sprains, strains, and disclocations, repetitive/overuse injuries, general aches and pains, contusions and trauma to such areas as hands, wrist, elbow, shoulder, neck, back, knees, ankles, feet and toes.

CONTRAINDICATIONS

Known sensitivity to any of the active or inactive ingredients of SpeedGel Rx®.

WARNINGS

For external use only. Direct patient not to ingest SPEEDGEL RX and to avoid contact with the eyes and mucous membranes, wounds, and damaged skin. If condition worsens, or if symptoms persist for more than seven days or clear up and occur again within a few days, patient should consult a doctor. If a rash develops, patient should discontinue use until rash clears. After the disappearance of rash, patient can try SPEEDGEL RX again on a test area and monitor the site for additional results. If no rash or redness results, then patient can resume use. However, if the rash persists or redevelops, use should be discontinued.

Direct patient to keep this product out of reach of children and seek medical help or contact a Poison Control Center immediately if swallowed.

PRECAUTIONS

Use in Pregnancy: No human or animal studies on the effect of SPEEDGEL RX in pregnancy have been conducted.

Nursing Mothers: It is not known whether SPEEDGEL RX is excreted in breast milk.

FEMALES & MALES OF REPRODUCTIVE POTENTIAL

No human or animal studies on the effect of SpeedGel Rx® in females & males of reproductive potential have been conducted.

ADVERSE REACTIONS

Rarely, allergic skin reactions may occur. If allergic reactions occur, discontinue use of the drug.

DOSAGE AND ADMINISTRATION

Apply 1 ml (4 pumps of the bottle) as a thin layer to the affected area 3-4 times daily and rub in gently (wash hands after application). Applications of less than 3-4 times daily will not produce optimum results. Excess amounts may be wiped from the area. Safe to use on children over the age of 2 years.

Applications of less than 3-4 times a day will not produce optimum results. Excess drops may be wiped from the area.

HOW SUPPLIED/STORAGE AND HANDLING

NDC 35781-0210-1 HOMEOPATHIC TRANSDERMAL PAIN RELIEF GEL RX ONLY NET CONTENTS 0.33 FL OZ (10 ML) Package Size: 0.33 fl oz (10ml) bottle NDC 35781-0210-2 HOMEOPATHIC TRANSDERMAL PAIN RELIEF GEL RX ONLY NET CONTENTS 1.01 FL OZ (30 ML) Package Size: 1.01 fl oz (30ml) bottle NDC 35781-0210-9 HOMEOPATHIC TRANSDERMAL PAIN RELIEF GEL RX ONLY NET CONTENTS 3.04 FL OZ (90 ML) Package Size: 3.04 fl oz (90ml) bottle Manufactured for: Manufactured for: Gensco Pharma, LLC 8550 NW 33rd Street, Suite 200. Miami, FL 33122 (855) 743-6726 www.genscopharma.com